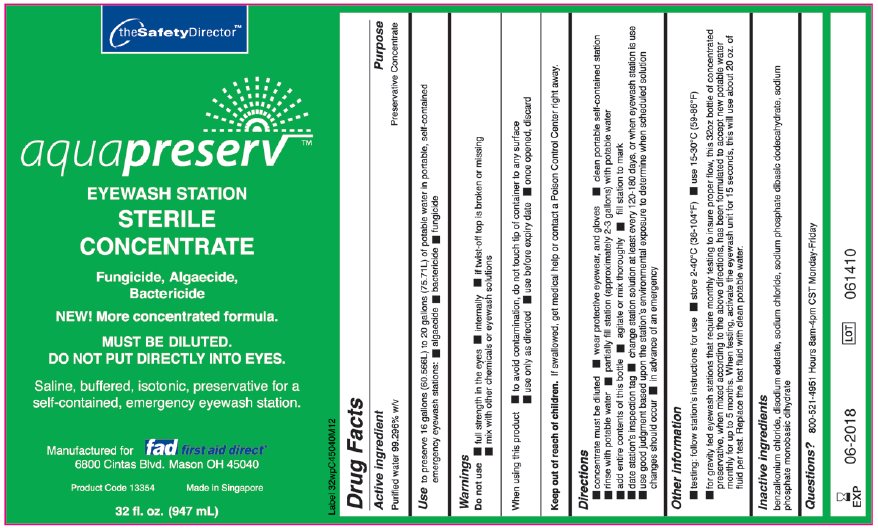 DRUG LABEL: theSafetyDirector aquapreserv
NDC: 42961-159 | Form: SOLUTION, CONCENTRATE
Manufacturer: Cintas Corporation
Category: otc | Type: HUMAN OTC DRUG LABEL
Date: 20140715

ACTIVE INGREDIENTS: WATER 992.96 g/1000 mL
INACTIVE INGREDIENTS: BENZALKONIUM CHLORIDE; EDETATE DISODIUM; SODIUM CHLORIDE; SODIUM PHOSPHATE, DIBASIC, DODECAHYDRATE; SODIUM PHOSPHATE, MONOBASIC, DIHYDRATE

Drug Facts

Active ingredient

Purified water 99.296% w/v

Purpose

Preservative Concentrate

Use

To preserve 16 gallons (60.566L) to 20 gallons (75.71L) of potable water in portable, self-contained emergency eyewash stations:

- algaecide
- bactericide
- fungicide

Warnings

Do not use

- full strength in the eyes
- internally
- if twist-off top is broken or missing
- mix with other chemicals or eyewash solutions

When using this product

- to avoid contamination, do not touch tip of container to any surface
- use only as directed
- use before expiry date
- once opened, discard

Keep out of reach of children. If swallowed, get medical help or contact a Poison Control Center right away.

Directions

- concentrate must be diluted
- wear protective eyewear, and gloves
- clean portable self-contained station
- rinse with potable water
- partially fill station (approximately 2-3 gallons) with potable water
- add entire contents of this bottle
- agitate or mix thoroughly
- fill station to mark
- date station’s inspection tag
- change station solution at least every 120-180 days, or when eyewash station is use
- use good judgment based upon the station’s environmental exposure to determine when scheduled solution changes should occur
- in advance of an emergency

Other information

- testing: follow station’s instructions for use
- store 2-40°C (36-104°F)
- use 15-30°C (59-86°F)
- for gravity fed eyewash stations that require monthly testing to insure proper flow, this 32oz bottle of concentrated preservative, when mixed according to the above directions, has been formulated to accept new potable water monthly for up to 5 months. When testing, activate the eyewash unit for 15 seconds, this will use about 20 oz of fluid per test. Replace the lost fluid with clean potable water.

Inactive ingredients

benzalkonium chloride, disodium edetate, sodium chloride, sodium phosphate dibasic dodecahydrate, sodium phosphate monobasic dihydrate

Questions?

800-521-4951 Hours 8am-4pm CST Monday-Friday

Package/Label Principal Display Panel

theSafetyDirectorTM

aquapreservTM

EYEWASH STATION STERILE CONCENTRATE

Fungicide, Algaecide, Bactericide

NEW! More concentrated formula.

MUST BE DILUTED.
DO NOT PUT DIRECTLY INTO EYES.

Saline, buffered, isotonic, preservative for a self-contained, emergency eyewash station.

Manufactured for fad first aid direct
6800 Cintas Blvd. Mason OH 45040

Product Code 13354

Made in Singapore

32 fl. oz. (947 mL)